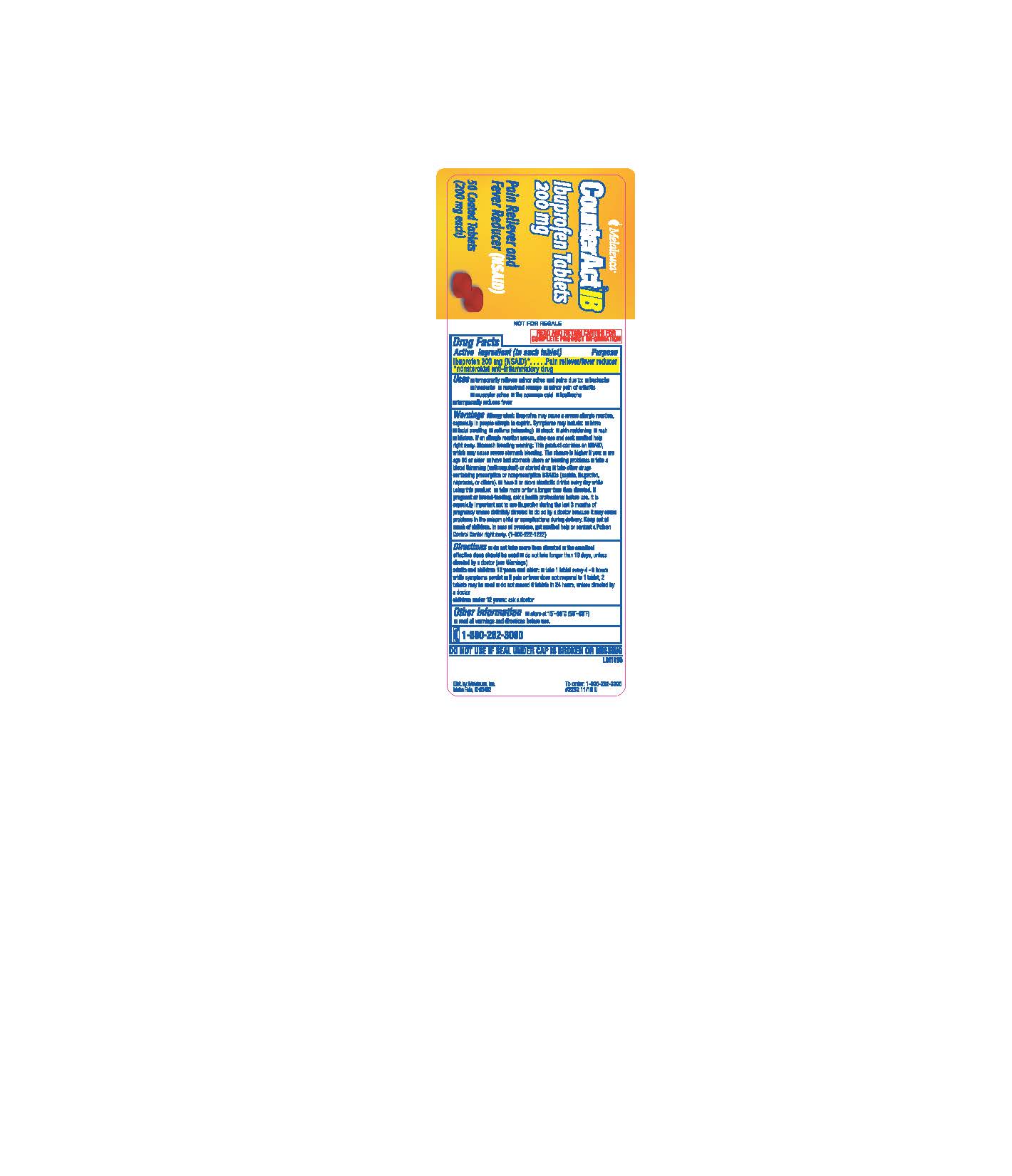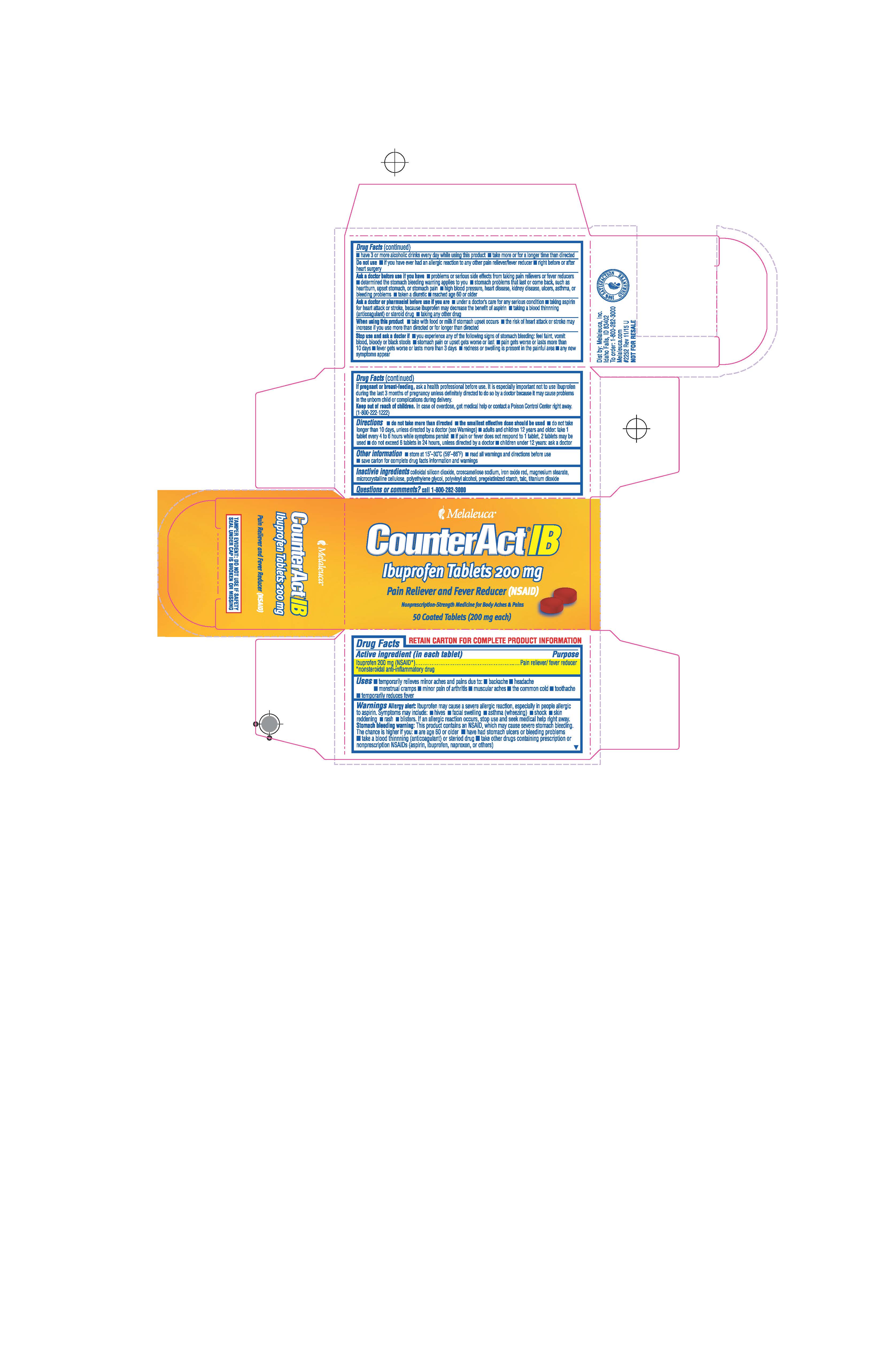 DRUG LABEL: CounterAct
NDC: 54473-308 | Form: TABLET, COATED
Manufacturer: Melaleuca, Inc
Category: otc | Type: HUMAN OTC DRUG LABEL
Date: 20230111

ACTIVE INGREDIENTS: IBUPROFEN 200 mg/1 1
INACTIVE INGREDIENTS: CROSCARMELLOSE SODIUM; TALC; SILICON DIOXIDE; HYPROMELLOSES; FERRIC OXIDE RED; MAGNESIUM STEARATE; CELLULOSE, MICROCRYSTALLINE; POLYETHYLENE GLYCOL; POLYVINYL ALCOHOL, UNSPECIFIED; STARCH, CORN; TITANIUM DIOXIDE

CounterAct IB Content of Label

Purpose
Pain reliever/fever reducer

Uses

- temporarily relieves minor aches and pains due to:
-
  - headache
  - muscular aches
  - minor pain of arthritis
  - toothache
  - backache
  - the common cold
  - menstrual cramps
- temporarily reduces fever

Do not use

- if you have ever had an allergic reaction to any other pain reliever/fever reducer
- right before or after heart surgery

Ask a doctor before use if

- you have problems or serious side effects from taking pain relievers or fever reducers
- the stomach bleeding warning applies to you
- you have a history of stomach problems such as heartburn
- you have high blood pressure, heart disease, liver cirrhosis, or kidney disease
- you have asthma
- you are taking a diuretic

Ask a doctor or pharmacist before use if you are

- taking aspirin for heart attack or stroke, because ibuprofen may decrease this benefit of aspirin
- under a doctor's care for any serious condition
- taking any other drug
- taking any other drug containing an NSAID (prescription or nonprescription)
- taking a blood thinning (anticoagulant) or steroid drug

When using this product

- take with food or milk if stomach upset occurs
- long term continuous use may increase the risk of heart attack or stroke

Stop use and ask a doctor if

- you experience any of the following signs of bleeding:
-
  - feel faint
  - vomit blood
  - have blood ro black stools
  - have stomach pain that does not get better
- pain gets worse or lasts more than 10 days
- fever gets worse or lasts more than 3 days
- redness or swelling is present in the painful area
- any new symptoms appear

PREGNANCY OR BREAST FEEDING

If pregnant or breast-feeding, ask a health professional before use. It is especially important not to use Ibuprofen during the last 3 months of pregnancy unless definitely directed to do so by a doctor because it may cause problems in the unborn child or complications during delivery.

Keep out of reach of children. In case of overdose, get medical help or contact a Poison Control Center right away (1-800-222-1222).

Directions

- do not take more than directed
- the smallest effective dose should be used

Adults and children 12 years and older:

- take 1 tablet every 4 to 6 hours while symptoms persist
- if pain or fever does not respond to 1 tablet, 2 tablets may be used
- do not exceed 6 tablets in 24 hours unless directed by a doctor
- Children under 12 years:
-
  - ask a doctor

Other information

- Store between 20 to 25°C (68 to 77°F)
- Read all warnings and directions before use
- save carton for complete drug facts information and warnings

INACTIVE INGREDIENT

Inactive ingredients collodial silicon dioide, croscarmellose sodium, iron oxide red, magnesium stearate, microcrystalline cellulose, polyethylene glycol, polyvinyl alcohol, pregelatinized starch, talc, titanium dioxide

Questions of comments? call 1-800-282-3000

BOXED WARNING

TAMPER EVIDENT: DO NOT USE IF IMPRINTED SAFETY SEAL UNDER CAP IS BROKEN OR MISSING